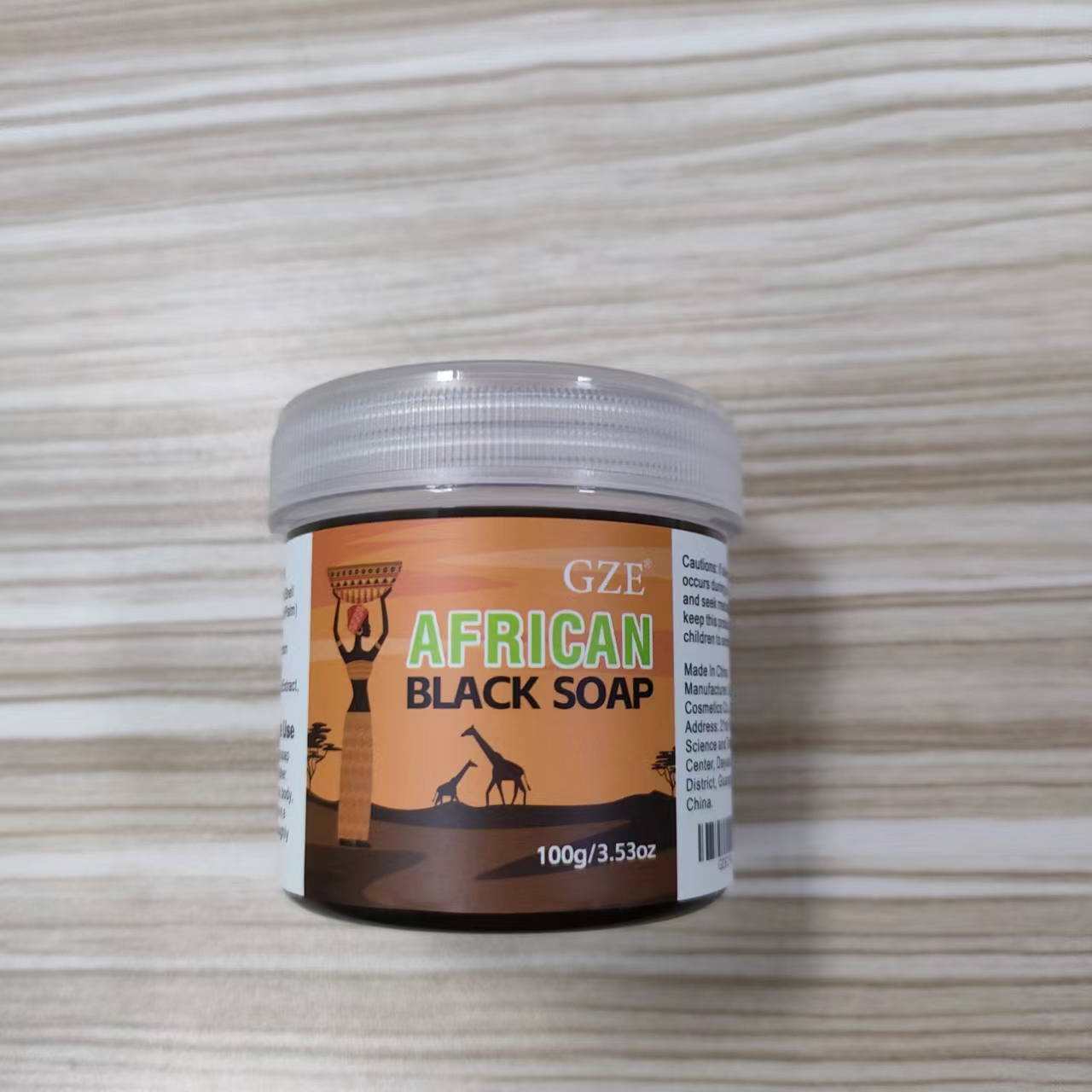 DRUG LABEL: GZE African BlackSoap
NDC: 74458-297 | Form: CREAM
Manufacturer: Guangzhou Yilong Cosmetics Co., Ltd
Category: otc | Type: HUMAN OTC DRUG LABEL
Date: 20241126

ACTIVE INGREDIENTS: TOCOPHEROL 5 g/100 g; COCOA SHELL 30 g/100 g
INACTIVE INGREDIENTS: ELAEIS GUINEENSIS (PALM) KERNEL OIL; BUTYROSPERMUM PARKII (SHEA) BUTTER; AQUA; COCOS NUCIFERA (COCONUT) OIL; MUSA PARADISIACA (BANANA) FRUIT EXTRACT

GZE AFRICAN BLACK SOAP

ACTIVE INGREDIENT

Theobroma Cacao (Cocoa) Shell Powder

Tocopherol

INACTIVE INGREDIENT

Theobroma Cacao (Cocoa) Shell Powder

Elaeis Guineensis (Palm) Kernel Oil

Cocos Nucifera (Coconut) Oil

Butyrospermum Parkii (Shea) Butter

Musa Paradisiaca (Banana) Fruit Extract

Aqua

Tocopherol

INDICATIONS AND USAGE

Wet your hands and rub the soap between
them to create a lather. Apply the lather to your face, body, or hair,
and gently massage in a circular motion. Rinse thoroughly with
warm water

DOSAGE AND ADMINISTRATION

Wet your hands and rub the soap between
them to create a lather. Apply the lather to your face, body, or hair,
and gently massage in a circular motion. Rinse thoroughly with
warm water

WARNINGS

For external use only.

Stop use and ask a doctor if rash occurs.

Do not use on damaged or broken skin.

When using this product keep out of eyes. Rinse with water to remove.

Keep out of reach of children. If swallowed, get medical help or contact a Poison Control Center right away.